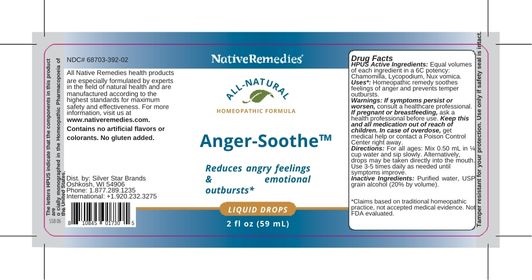 DRUG LABEL: NativeRemedies Anger-Soothe
NDC: 68703-392 | Form: LIQUID
Manufacturer: Silver Star Brands
Category: homeopathic | Type: HUMAN OTC DRUG LABEL
Date: 20250101

ACTIVE INGREDIENTS: STRYCHNOS NUX-VOMICA SEED 6 [hp_C]/59 mL; MATRICARIA RECUTITA 6 [hp_C]/59 mL; LYCOPODIUM CLAVATUM SPORE 6 [hp_C]/59 mL
INACTIVE INGREDIENTS: WATER; ALCOHOL

NativeRemedies® Anger-Soothe™

HPUS Active Ingrediients

HPUS Active Ingredients: Equal volumes of each ingredient in a 6C potency: Chamomilla, Lycopodium, Nux vomica.

The letters HPUS indicate that the components in this product are offically monographed in the Homeopathic Pharmacopoeia of the United States.

Uses*:

Uses*: Homeopathic remedy soothes feelings of anger and prevents temper outbursts.

*Claims based on traditional homeopathic practice, not accepted medical evidence. Not FDA evaluated.

Warnings

Warnings: If symptoms persist or worsen, consult a healthcare professional. If pregnant or breastfeeding, ask a health professional before use. Keep this and all medication out of reach of children. In case of overdose, get medical help or contact a Poison Control Center right away.

Directions

Directions: For all ages: Mix 0.50 mL in 1/4 cup water and sip slowly. Alternatively, drops may be taken directly into the mouth. Use 3-5 times daily as needed until symptoms improve.

OTHER SAFETY INFORMATION

Contains no artificial flavors or colorants. No gluten added.

Tamper resistant for your protection. Use only if safety seal is intact.

Inactive Ingredients

Inactive Ingredients: Purified water, USP grain alcohol (20% by volume).

KEEP OUT OF REACH OF CHILDREN

Keep this and all medication out of reach of children. In case of overdose, get medical help or contact a Poison Conrtol Center right away.

PREGNANCY OR BREAST FEEDING

If pregnant or breastfeeding, ask a health professional before use.

PURPOSE

Reduces angry feelings & emotional outbursts.